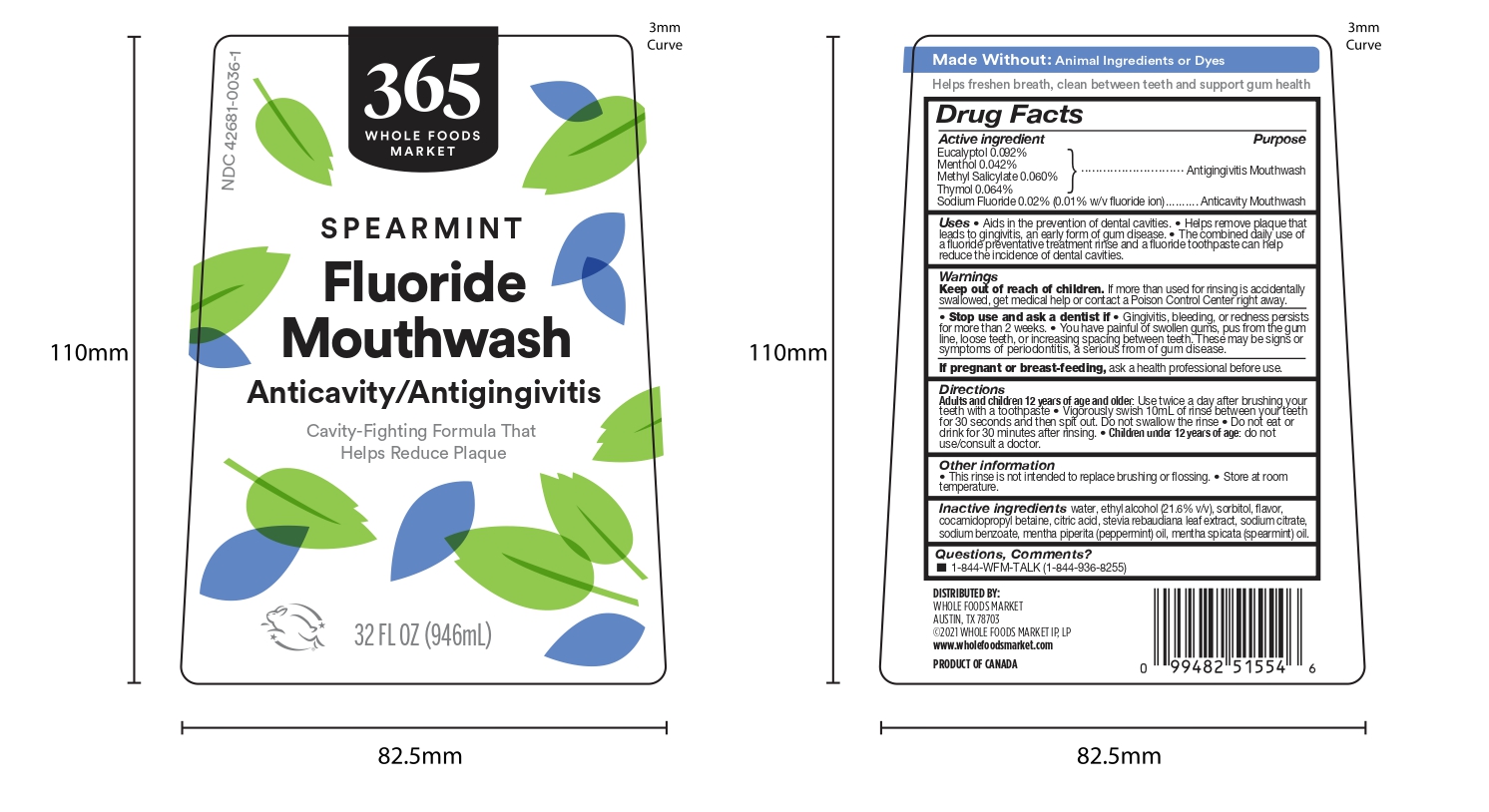 DRUG LABEL: 365 Whole Foods Market Anticavity/Antigingivitis Mouthwash
NDC: 42681-0036 | Form: MOUTHWASH
Manufacturer: Whole Foods Market, Inc.
Category: otc | Type: HUMAN OTC DRUG LABEL
Date: 20220512

ACTIVE INGREDIENTS: METHYL SALICYLATE 0.6 mg/1 mL; SODIUM FLUORIDE 0.1 mg/1 mL; MENTHOL 0.42 mg/1 mL; THYMOL 0.64 mg/1 mL; EUCALYPTOL 0.92 mg/1 mL
INACTIVE INGREDIENTS: SORBITOL; SODIUM BENZOATE; ALCOHOL; WATER; COCAMIDOPROPYL BETAINE; SODIUM CITRATE; ANHYDROUS CITRIC ACID; PEPPERMINT OIL; SPEARMINT OIL; STEVIA LEAF

WFM PLD Listing Mouthwash with Fluoride

ACTIVE INGREDIENT

Eucalyptol 0.092%

Menthol 0.042%

Methyl Salicylate 0.060%

Thymol 0.064%

Sodium Fluoride 0.02% (0.01% w/v fluoride ion)

DOSAGE AND ADMINISTRATION

Directions Adults and children 12 years of age and older: Use twice a day after brushing your teeth with a toothpaste • Vigorously swish 10mL of rinse between your teeth for 30 seconds and then spit out. Do not swallow the rinse • Do not eat or drink for 30 minutes after rinsing. • Children under 12 years of age: do not use/consult a doctor.

WARNINGS

Keep out of reach of children. If more than used for rinsing is accidentally swallowed, get medical help or contact a Poison Control Center right away.

• Stop use and ask a dentist if • Gingivitis, bleeding, or redness persists for more than 2 weeks. • You have painful of swollen gums, pus from the gum line, loose teeth, or increasing spacing between teeth. These may be signs or symptoms of periodontitis, a serious from of gum disease.

PREGNANCY OR BREAST FEEDING

If pregnant or breast-feeding, ask a health professional before use.

INACTIVE INGREDIENT

Inactive ingredients: water, ethyl alcohol (21.6% v/v), sorbitol, flavor, cocamidopropyl betaine, citric acid, stevia rebaudiana leaf extract, sodium citrate, sodium benzoate, mentha piperita (peppermint) oil, mentha spicata (spearmint) oil.

RECENT MAJOR CHANGES

Highlights:

• Dosage and Administration 24 Jan 2022

INDICATIONS AND USAGE

Uses • Aids in the prevention of dental cavities. • Helps remove plaque that leads to gingivitis, an early form of gum disease. • The combined daily use of a fluoride preventative treatment rinse and a fluoride toothpaste can help reduce the incidence of dental cavities.

PURPOSE

Uses • Aids in the prevention of dental cavities. • Helps remove plaque that leads to gingivitis, an early form of gum disease. • The combined daily use of a fluoride preventative treatment rinse and a fluoride toothpaste can help reduce the incidence of dental cavities.